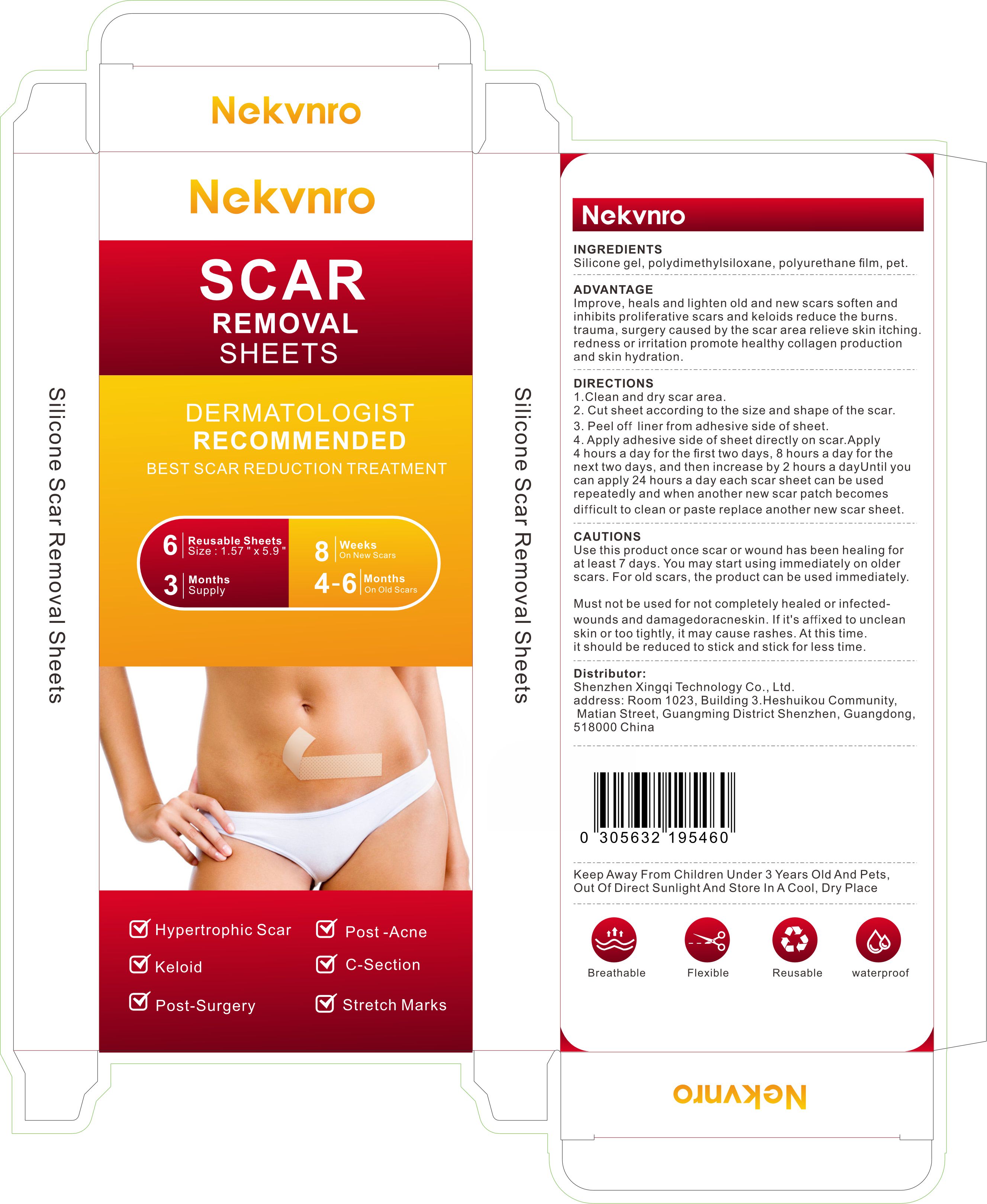 DRUG LABEL: Nekvnro SCAR REMOVAL SHEETS
NDC: 84613-058 | Form: PATCH
Manufacturer: Shenzhen Xingqi Technology Co., Ltd.
Category: otc | Type: HUMAN OTC DRUG LABEL
Date: 20240913

ACTIVE INGREDIENTS: SILICON DIOXIDE 1 g/1 g
INACTIVE INGREDIENTS: POLYURETHANE-39; PEGOTERATE; DIMETHICONE

ACTIVE INGREDIENT

Silicone gel 1%

Purpose

SCAR REMOVAL SHEETS

Uses

1.Clean and dry scar area.
2. Cut sheet according to the size and shape of the scar.
3. Peel off liner from adhesive side of sheet.
4. Apply adhesive side of sheet directly on scar.Apply 4 hours a day for the first two days, 8 hours a day for the next two days, and then increase by 2 hours a dayUntil you can apply 24 hours a day each scar sheet can be used repeatedly and when another new scar patch becomes difficult to clean or paste replace another new scar sheet.

WARNINGS

Use this product once scar or wound has been healing for at least 7 days. You may start using immediately on older scars. For old scars, the product can be used immediately.

Must not be used for not completely healed or infected- wounds and damagedoracneskin. If it's affixed to unclean
skin or too tightly, it may cause rashes. At this time. it should be reduced to stick and stick for less time.

Dosage and administration

For external use only.

When using section

Use this product once scar or wound has been healing for at least 7 days. You may start using immediately on older scars. For old scars, the product can be used immediately.

Must not be used for not completely healed or infected-wounds and damagedoracneskin. If it's affixed to unclean skin or too tightly, it may cause rashes. At this time. it should be reduced to stick and stick for less time

stop use

on broken or irritated scalp

Keep out of reach of children.

Keep Away From Children Under 3 Years Old And Pets,
Out Of Direct Sunlight And Store In A Cool, Dry Place

Inactive ingredients

polydimethylsiloxane, polyurethane film, pet.